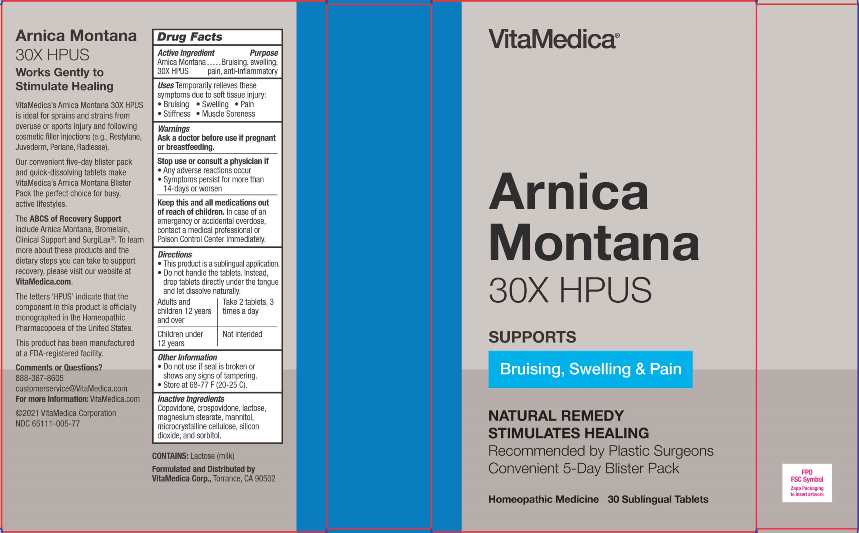 DRUG LABEL: ARNICA MONTANA
NDC: 65111-005 | Form: TABLET
Manufacturer: VITAMEDICA INC
Category: homeopathic | Type: HUMAN OTC DRUG LABEL
Date: 20220518

ACTIVE INGREDIENTS: ARNICA MONTANA 30 [hp_X]/1 1
INACTIVE INGREDIENTS: SORBITOL; SILICON DIOXIDE; CROSPOVIDONE; COPOVIDONE; LACTOSE; MAGNESIUM STEARATE; MANNITOL; CELLULOSE, MICROCRYSTALLINE

DRUG FACTS:

ACTIVE INGREDIENT:

Arnica Montana 30X.

PURPOSE:

Temporarily relieves these symptoms due to soft tissue injury:

• Bruising • Swelling • Pain

• Stiffness • Muscle Soreness

WARNINGS:

Ask a doctor before use if pregnant or breastfeeding.

Stop use and ask a doctor if

• Any adverse reactions occur

• Symptoms persist for more than 14-days or worsen

Keep this and all medications out of reach of children.

In case of an emergency or accidental overdose, contact a medical professional or Poison Control Center immediately.

KEEP OUT OF REACH OF CHILDREN:

Keep this and all medications out of reach of children.

In case of an emergency or accidental overdose, contact a medical professional or Poison Control Center immediately.

DIRECTIONS:

• This product is a sublingual application.

• Do not handle the tablets. Instead, drop tablets directly under the tongue and let dissolve naturally.

Adults and children 12 years and over. Take 2 tablets, 3 times a day.

Not intended for children under 12 years of age.

INDICATIONS:

Temporarily relieves these symptoms due to soft tissue injury:

• Bruising • Swelling • Pain

• Stiffness • Muscle Soreness

OTHER INFORMATION:

• Do not use if seal is broken or shows any signs of tampering.

• Store at 68-77 F (20-25 C).

INACTIVE INGREDIENTS:

Copovidone, Crospovidone, Lactose, Magnesium Stearate, Mannitol, Microcrystalline Cellulose, Silicon Dioxide, Sorbitol.

QUESTIONS:

Formulated and Distributed by

VitaMedica Corp.,

Torrance, CA 90502

888-367-8605

customerservice@VitaMedica.com

For more Information : VitaMedica.com

©2021 Vita Medica Corporation

NDC 65111-005-77

PACKAGE LABEL DISPLAY:

VitaMedica

Arnica

Montana

30X HPUS

SUPPORTS

Bruising, Swelling & Pain

NATURAL REMEDY

STIMULATES HEALING

Recommended by Plastic Surgeons

Convenient 5-Day Blister Pack

Homeopathic Medicine

30 Sublingual Tablets